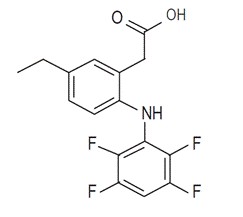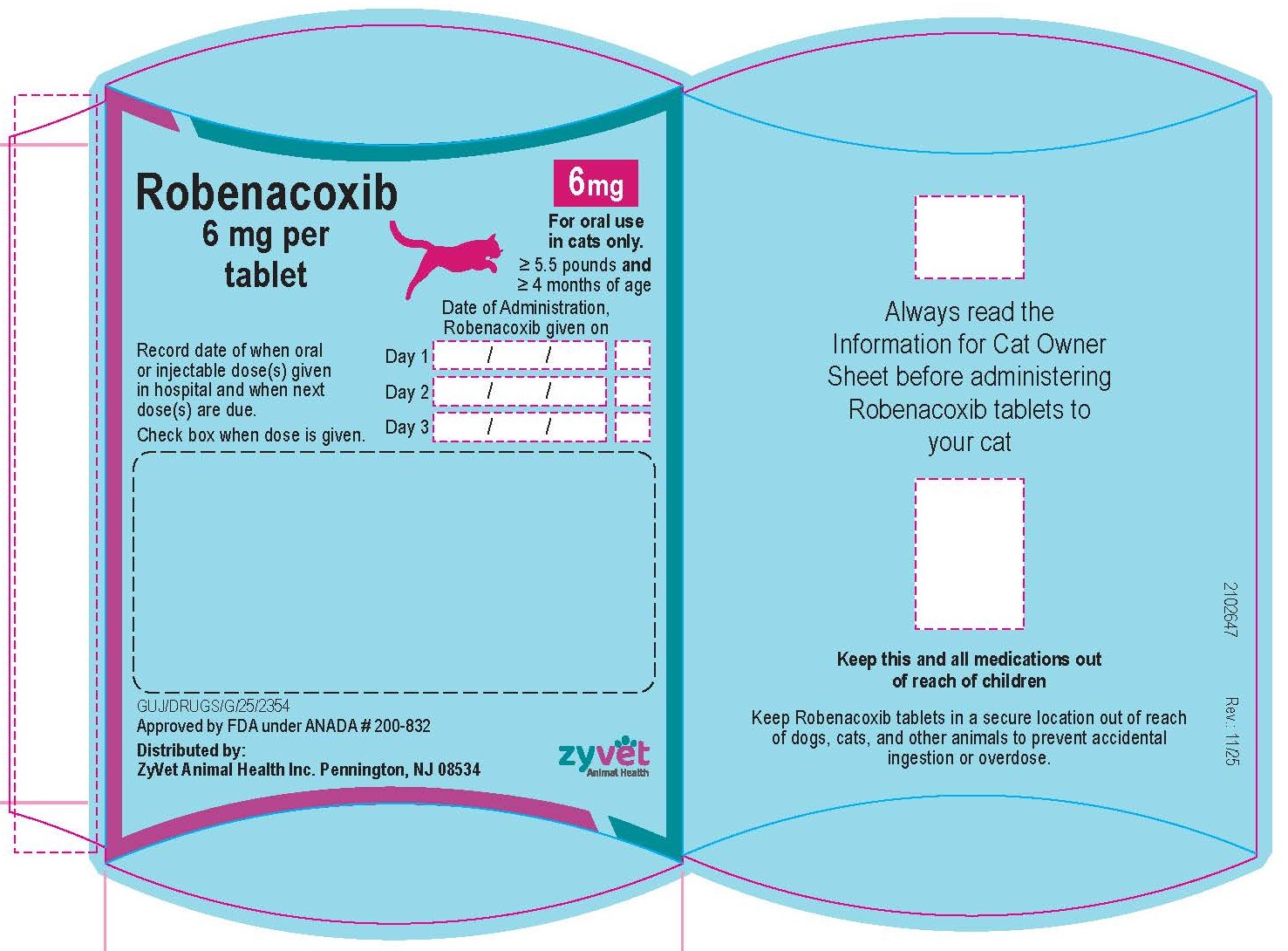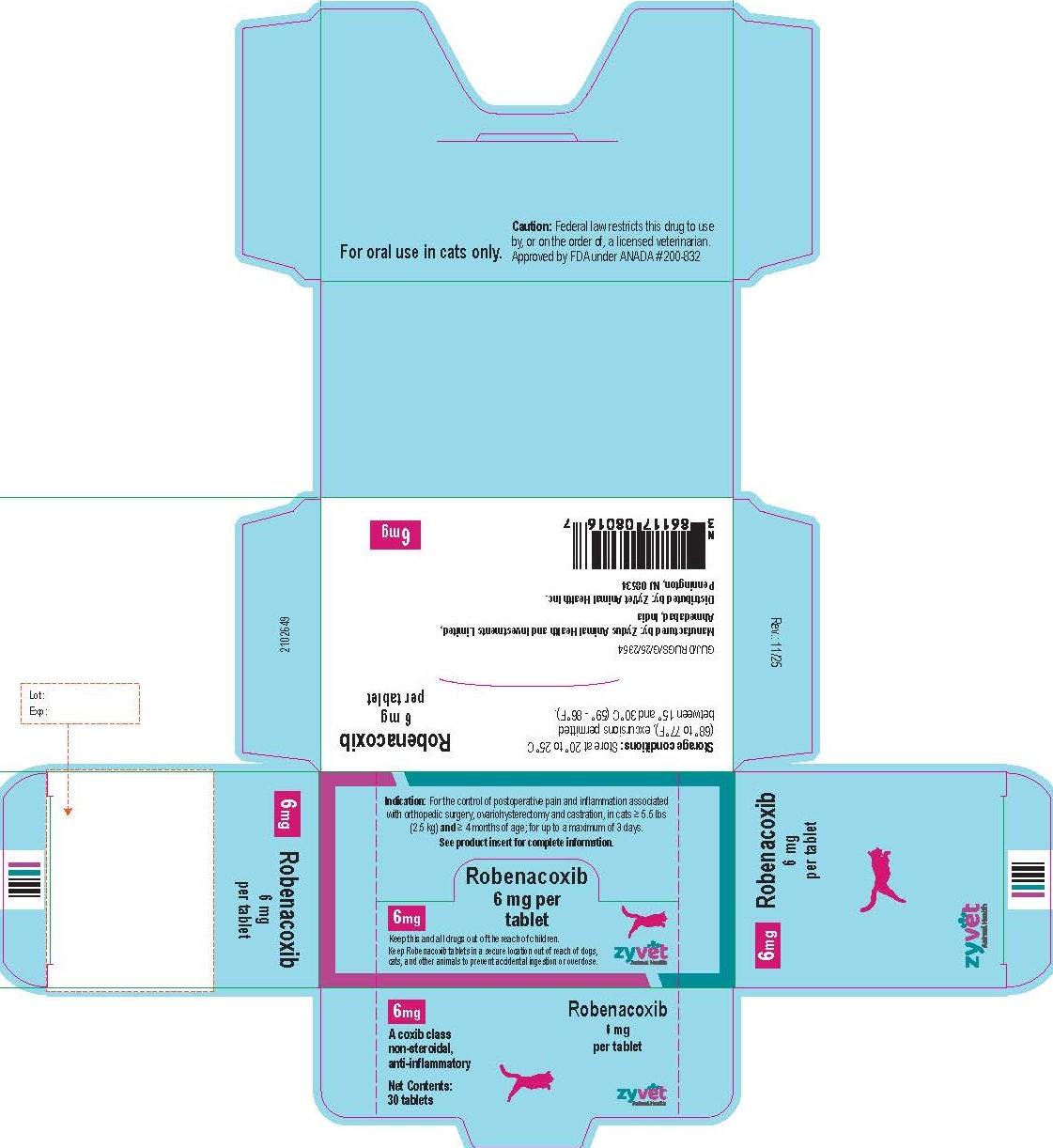 DRUG LABEL: ROBENACOXIB
NDC: 86117-080 | Form: TABLET
Manufacturer: ZYVET ANIMAL HEALTH INC.
Category: animal | Type: PRESCRIPTION ANIMAL DRUG LABEL
Date: 20260121

ACTIVE INGREDIENTS: ROBENACOXIB 6 mg/1 1

Robenacoxib
6 mg Tablets for Cats

For Oral Use In Cats Only

Caution:

Federal law restricts this drug to use by or on the order of a licensed veterinarian.

Description:

Robenacoxib is a non-narcotic, non-steroidal anti-inflammatory drug (NSAID) of the coxib class. Tablets are round, off white to beige colored, speckled, not scored, flavored and contain 6 mg robenacoxib. The molecular weight of robenacoxib is 327.28. The empirical formula is C16-H13-F4-NO2.

Robenacoxib is [5-Ethyl-2-(2,3,5,6-tetrafluoro-phenylamino)-phenyl]-acetic acid. The structural formula is:

Indication:

Robenacoxib tablets are indicated for the control of postoperative pain and inflammation associated with orthopedic surgery, ovariohysterectomy and castration, in cats ≥ 5.5 lbs (2.5 kg) and ≥ 4 months of age; for up to a maximum of 3 days.

Dosage and Administration:

Always provide "Information for Cat Owners" Sheet with prescription. Carefully consider the potential benefits and risks of Robenacoxib tablets and other treatment options before deciding to use Robenacoxib tablets.

Use the lowest effective dose for the shortest duration consistent with individual response.

The dose of Robenacoxib tablets is 0.45 mg/lb (1 mg/kg) orally once daily, for a maximum of 3 days. See dosing chart for dosage directions.

Dosage Directions: For oral use in cats ≥ 5.5 lbs and ≥ 4 months of age; for up to a maximum of 3 days. Tablets are not scored and should not be broken.

Body weight | 6 mg Robenacoxib Tablets
5.5 to 13.2 lbs (2.5 to 6 kg) | 1 whole tablet once daily
13.3 to 26.4 lbs (6.1 to 12 kg) | 2 whole tablets once daily

Do not use in cats weighing less than 5.5 lbs, as cats less than 5.5 lbs cannot be accurately dosed.

The first dose should be administered approximately 30 minutes prior to surgery, at the same time as the pre-anesthetic agents are given.

Robenacoxib tablets may be given with or without food.

In cats ≥ 5.5 lbs and ≥ 4 months of age, subsequent doses can be given via the oral tablet, or interchanged with subcutaneous injection for a maximum of 3 total robenacoxib doses over 3 days, not to exceed one dose per day (see Animal Safety and the robenacoxib injection package insert).

Note the dose of Robenacoxib tablets and robenacoxib injection are different.

If a second and third tablet dose is dispensed to the client to administer at home, doses should be dispensed in the dispensing envelope with the attached Information for Owner Sheet intact. Do not remove Information for Cat Owner Sheet. Record when the first dose was administered on the dispensing envelope. Cats weighing ≥ 13.3 lbs may require two blister cards, each dispensed in an individual dispensing envelope.

Contraindications:

Robenacoxib tablets should not be used in cats that have a hypersensitivity to robenacoxib or known intolerance to NSAIDs.

Warnings:

Not for use in humans. Keep this and all medications out of reach of children. Consult a physician in case of accidental ingestion by humans. For oral use in cats only.

All cats should undergo a thorough history and physical examination before the initiation of NSAID therapy. Appropriate laboratory tests should be conducted to establish hematological and serum biochemical baseline data prior to administration of an NSAID.

Owners should be advised to observe for signs of potential drug toxicity (see Adverse Reactions and Animal Safety) and be given an "Information for Cat Owners" Sheet about Robenacoxib tablets.

Do not administer robenacoxib tablets or injection in conjunction with any other oral or injectable NSAID or corticosteroid.

Keep Robenacoxib tablets in a secure location out of reach of dogs, cats, and other animals to prevent accidental ingestion or overdose.

Precautions:

When using NSAIDS such as Robenacoxib, the use of fluid therapy during surgery is recommended to decrease potential renal complications (see Adverse Reactions, Post-Approval Experience).

Appetite should be monitored in cats receiving Robenacoxib.

Stop administration of Robenacoxib if appetite decreases or if the cat becomes lethargic.

The use of Robenacoxib tablets has not been evaluated in cats younger than 4 months of age and weighing less than 5.5 lbs, cats used for breeding, or in pregnant or lactating cats. Cats receiving Robenacoxib should weigh at least 5.5 lbs.

The use of Robenacoxib in cats with cardiac disease has not been studied. Robenacoxib has been shown to prolong the QT interval.

As a class, cyclo-oxygenase inhibitory NSAIDs may be associated with gastrointestinal, renal, and hepatic toxicity. Sensitivity to drug-associated adverse events varies with the individual patient. Cats that have experienced adverse reactions from one NSAID may experience adverse reactions from another NSAID. Patients at greatest risk for adverse events are those that are dehydrated, on concomitant diuretic therapy, or those with existing renal, cardiovascular, and/or hepatic dysfunction. Anesthetic drugs may affect renal perfusion; approach concomitant use of anesthetics and NSAIDs cautiously. Appropriate monitoring procedures (including ECG, blood pressure, and temperature regulation) should be employed during all surgical procedures. The use of parenteral fluids during surgery is recommended to decrease potential renal complications when using NSAIDs perioperatively.

If additional pain medication is needed after a daily dose of Robenacoxib, a non-NSAID/non-corticosteroid class of analgesic may be necessary. Concurrent administration of potentially nephrotoxic drugs should be carefully approached and monitored. NSAIDs may inhibit prostaglandins which maintain normal homeostatic function. Such anti-prostaglandin effects may result in clinically significant disease in patients with underlying or pre-existing disease that has not been previously diagnosed. NSAIDs possess the potential to produce gastrointestinal ulcerations and/ or gastrointestinal perforations. Do not use Robenacoxib concomitantly with other anti-inflammatory drugs, such as NSAIDs or corticosteroids. Consider appropriate washout times when switching from one NSAID to another or when switching from corticosteroid use to NSAID use. Robenacoxib tablets and robenacoxib injection are safe to use interchangeably when given once a day for a maximum of 3 days in cats ≥ 4 months of age and ≥ 5.5 lbs. Note the dose of Robenacoxib tablets and robenacoxib injection are different.

The use of concomitantly protein-bound drugs with robenacoxib has not been studied in cats. Commonly used protein-bound drugs include cardiac, anticonvulsant and behavioral medications. The influence of concomitant drugs that may inhibit metabolism of robenacoxib has not been evaluated. Drug compatibility should be monitored in patients requiring adjunctive therapy. Concurrent medications used during the field study with robenacoxib tablets included antiparasiticides, anesthetics, pre-anesthetic medications, and antibiotics.

The effect of cyclo-oxygenase inhibition and the potential for thromboembolic occurrence or a hypercoagulable state has not been evaluated. It is unknown whether cats with a history of hypersensitivity to ß lactam drugs will exhibit hypersensitivity to Robenacoxib. Robenacoxib is poorly soluble in water and in acid solutions readily degrades to form γ-lactam. In cats, lactam is a metabolite of robenacoxib. Additionally, lactam is a degradation product that increases over the shelf-life of the tablets. Neurologic signs have been associated with the use of ß lactam drugs; it is unknown if the lactam in robenacoxib may cause similar neurologic signs (see Animal Safety). Occurrences of seizures, ataxia, and nystagmus have been associated with the use of robenacoxib.

Robenacoxib may prolong the QT interval; the associated risk of developing ventricular arrhythmia is unknown. The use of robenacoxib with other drugs shown to prolong the QT interval is not recommended.

Commonly used drugs that prolong the QT interval include antihistamines, prokinetic drugs, and certain anesthetic drugs. As a class, it is unknown if the use of NSAIDs in asthmatic cats can cause acute exacerbations, as seen in some humans.

Adverse Reactions:

In a controlled field study, a total of 249 male and female cats representing 6 breeds, 6 months to 13 years old, weighing 5.5 – 15 lbs were included in the field safety analysis.

The following table shows the number of cats exhibiting each observation.

Adverse Reactions in the Postoperative Pain Field Study^1
Adverse Reaction | Robenacoxib 6 mg Tablets for Cats (robenacoxib) n = 167 | Placebo (vehicle control) n = 82
Incision site bleeding | 7 | 1
Incision site infection | 6 | 2
Inappetance, weight loss | 4 | 2
Decreased activity, lethargy | 4 | 1
Vomiting | 4 | 1
Cystitis, hematuria | 3 | 0
Hematachezia, diarrhea | 3 | 1
Hair loss, excoriation, bruising | 2 | 0
Respiratory, cardiac arrest | 1 | 0
Incoordination, weakness | 1 | 1
Death | 0 | 1
^1 Cats may have experienced more than one of these signs during the study.

The most commonly reported adverse reactions were surgical site bleeding, infected surgery sites, lethargy, vomiting and inappetance. Changes in the clinical pathology values were not considered clinically significant.

Post Approval Experience (2015)

The following adverse events are based on voluntary, post approval reporting. Not all adverse events are reported to FDA/CVM. It is not always possible to reliably estimate the adverse event frequency or establish a causal relationship to product exposure using these data. The signs reported are listed in decreasing order of reporting frequency:

Anorexia, depression/ lethargy, vomiting, elevated BUN, elevated creatinine, renal insufficiency/ failure, diarrhea, weight loss, dehydration.

In some cases, death has been reported. Some of these cases involved patients that developed renal failure/renal insufficiency.

Contact Information:

To report suspected adverse drug experiences, for technical assistance or to obtain a copy of the Safety Data Sheet (SDS), contact ZyVet Animal Health Inc. at 1-877-779-9838.

For additional information about adverse drug experience reporting for animal drugs, contact FDA at 1-888-FDA-VETS or http://www.fda.gov/reportanimalae

Information for Cat Owners:

Robenacoxib, like other drugs of its class, is not free from adverse reactions. Owners should be advised of the potential for adverse reactions and be informed of the clinical signs associated with drug intolerance. Adverse reactions may include vomiting, diarrhea, decreased appetite, dark or tarry stools, increased water consumption, increased urination, anemia, yellowing of gums, skin or white of the eye due to jaundice, lethargy, incoordination, seizure, or behavioral changes. Serious adverse reactions associated with this drug class can occur without warning and may result in death (see Warnings and Adverse Reactions). Owners should be advised to discontinue Robenacoxib tablets and contact their veterinarian immediately if signs of intolerance are observed. The vast majority of patients with drug related adverse reactions have recovered when the signs are recognized, the drug is withdrawn, and veterinary care, if appropriate, is initiated.

Clinical Pharmacology:

In an inflammation model in cats, robenacoxib had analgesic, antiinflammatory and anti-pyretic actions with a rapid onset of action (0.5 h).^1 In an in vitro whole blood assay in cats, robenacoxib demonstrated selective COX-2 inhibition.^2 The clinical relevance of this data has not been shown. Robenacoxib is an analog of diclofenac.

Absorption

After oral administration of robenacoxib tablets at 1 mg/kg without food, peak blood concentrations are attained rapidly with a median Tmax of 0.5 h, a mean Cmax of 1159 ng/ml and a mean AUC of 1337 ng.h/ml.

Co-administration of robenacoxib tablets with one third of the daily food ration produced no change in median Tmax (0.5 h), mean Cmax (1201 ng/ml) or mean AUC (1383 ng.h/ml). Co-administration of robenacoxib tablets with the entire daily food ration produced no delay in median Tmax (0.5 h), but a lower mean Cmax (691 ng/ml) and a lower mean AUC (1069 ng.h/ml). The systemic mean bioavailability of robenacoxib tablets was 49% without food. The pharmacokinetics of robenacoxib does not differ between male and female cats.

Distribution

Robenacoxib has a relatively small volume of distribution (mean Vss = 190 ml/kg) and is highly bound to plasma proteins (>99%). Robenacoxib persists longer in the inflammatory exudate of a tissue cage model than in blood. The median robenacoxib elimination half-life in exudate was about 27 hours versus 2.5 hours for blood.

Metabolism

Robenacoxib is extensively metabolized by the liver in cats. The systemic exposure of lactam metabolite is about 25% of robenacoxib exposure following oral administration to fed cats. Further, the systemic exposure to lactam appears to be two-fold greater in fed cats than fasted cats. Apart from one lactam metabolite, the identity of other metabolites is not known in cats.

Elimination

Robenacoxib is rapidly cleared from blood (mean clearance [CL] = 0.44 L kg/h) with an elimination mean half-life (t1/2) of 1.1 hours after intravenous administration. After oral administration of tablets, the terminal mean t1/2 from blood was 1.7 hours. Elimination, occurs predominantly through the biliary route (fecal and urinary excretion are 60 and 16.5% respectively).

Animal Safety:

21 Day Target Animal Safety Study: In a 21-day laboratory tolerance study, 8 month-old healthy, DSH cats (4/sex/group) were administered robenacoxib at a dose of 0 mg/kg or 24 mg/kg/day (10X the maximum exposure based on the single, 6 mg tablet size). All cats survived to study termination. Vomiting and decreased activity was noted in some of the treated cats. Two cats in the 10X group exhibited abnormal rear limb neurologic function. One of these cats also exhibited a head tilt and nystagmus at the end of the study. Mean food consumption was less in the 10X group. The mean kidney weights were lower in the 10X group compared to the control group; and the mean thymus weights were also lower in the 10X group compared to the controls. Two cats in the 10X group had chronic interstitial nephritis on histopathology. One 10X cat had a focal cecal/large intestinal erosion. One 10X cat and one control cat had periportal, multifocal necrosis in one lobe of the liver. There were four 10X cats and 2 control cats with renal tubular degeneration. Under the conditions of this study, robenacoxib was well tolerated when administered at 24 mg/kg/day for 21 days, except for 2 cats in the 10X group with neurologic signs.

42 Day Target Animal Safety Study:

In a 42 day study, 8 month-old, healthy cats were administered robenacoxib at 0, 2, 6 or 10 mg/kg/twice daily. Small thymuses were noted in all robenacoxib-treated groups with corresponding organ weight decreases and/or atrophic changes on histopathology. There was a decrease in the kidney weights in the 10 mg/kg/twice daily-group compared to the controls. Vomiting was the most common adverse reaction noted in the treated cats. An adequate safety margin was demonstrated for robenacoxib tablets when administered under the conditions of this 42-day study.

6 Month Target Animal Safety Study:

In a 6 month study, 8 month-old, healthy cats (4/sex/group) were administered robenacoxib at 0, 1X (2.4 mg/kg), 3X (7.2 mg/kg) or 5X (12 mg/kg) once daily. One 5X cat had clonic seizures on Day 115 and was ataxic on Day 175. One 5X cat had skin cold to the touch on Day 106. One cat in the 1X group experienced urethral obstruction/FLUTD. Vomiting, decreased activity, injected sclera and soft stools were the most common adverse reactions observed in the treated groups. Soft stools and injected sclera were also observed in the control group.

The mean body weights in the 1X and 3X groups were lower than the controls from Day 21 – Day 182; and lower in the 5X group from Day 28 – Day 182. There was a clear dose-related and possibly time-related increase in the QTc interval at Day 41 and Day 175, particularly in the 3X and 5X groups, no other ECG abnormalities were noted.

There was no obvious accumulation in Cmax or AUC between Days 1, 31 and 171, and there was no apparent difference in parameters between males and females. The following parameters were calculated for the 1X dosage: Tmax was 0.5 h (median), the dose-normalized mean Cmax was 668 ng/mL and the dose-normalized mean area under the curve (AUC(0-inf)) was 902 h*ng/mL. Similarly, the following parameters were calculated for the 3X dosage: Tmax was 0.5 h (median), the dose-normalized mean Cmax was 1019 ng/mL and the dose-normalized mean area under the curve (AUC(0-inf)) was 1394 h*ng/mL. For the 5X dosage the following parameters were calculated: Tmax was 1.0 h (median), the dose-normalized mean Cmax was 1198 ng/mL and the dose-normalized mean area under the curve (AUC(0-inf)) was 1884 h*ng/mL. A post hoc analysis of PK parameters revealed that dose normalized Cmax and AUC were greater than dose proportional.

The mean kidney weights were lower in all robenacoxib-treated groups. One 5X cat with decreased kidney weight and size also had transient increases in BUN and creatinine. There were transient increases in AST, amylase, and ALT in the 3X and 5X cats from Day 30 – Day 183. There was an increased severity of the tubular degeneration/regeneration in the kidneys of two 1X and two 5X cats with inflammation, papillary necrosis and papillary mineralization.

An increased incidence of minimal to mild Kupffer cell pigmentation was observed in the livers of all robenacoxib-treated cats; however, no hepatocellular damage was noted on histopathology. One 5X cat had a focal, minimal ulcer of the gastric fundus (peptic and parietal cells).

This 6 month safety study supports the safe use of robenacoxib tablets for the control of postoperative pain and inflammation associated with orthopedic surgery, ovariohysterectomy and castration in cats for a maximum of 3 days.

Interchangeable Use Safety Study:

Robenacoxib was administered orally (6 mg tablets) and subcutaneously (20 mg/mL solution) to 4-month old healthy cats at 0, 1, 2, and 3 times the labeled doses (1X = 2.4 mg/kg/day orally based on the inherent tablet dose band or 2.0 mg/kg/day subcutaneously). Interchangeable use was evaluated by alternating three 7-day oral tablet/3-day subcutaneous injection cycles followed by one final 7-day oral tablet dosing cycle. All cats survived until study termination. Findings included: elevated creatine kinase levels on Days 13 and 37, soft stools, histologic observation of a minimal oral (tongue) ulceration in a 1X cat, injection site edema for up to 120 hours prior to resolution, and a prolonged QT interval in treated cats as compared to the controls on Day 36. There was a dose dependent and statistically significant increase in the QT interval at all three robenacoxib tablets/ robenacoxib injection treatment levels. It is unknown if the increased QT interval suggests an elevated risk of ventricular arrhythmia or torsade de pointes in cats. In addition, a longer PR interval was noted in 1X group females on Day 36 compared to the controls. One 2X cat vomited twice during the last 2 dosing days. Histologically, the injection sites had minimal or mild, subacute/chronic inflammation. Inflammation at the injection sites was observed in both treated and control animals with a greater frequency in the higher dose groups than in the control and 1X groups.

Dose-normalized AUC and concentration levels were higher following the oral route than the subcutaneous route. There was no significant accumulation following once daily administration. One 2X-treated cat had a 7-fold increase in buccal mucosal bleeding time (BMBT) during the treatment period compared to the pre-treatment value.

Effectiveness:

Effectiveness was demonstrated using robenacoxib tablets in a masked, placebo-controlled, multi-site field study involving client-owned cats. In this study, 249 cats presenting for ovariohysterectomy or castration in conjunction with an onychectomy (forelimbs only) were randomly administered robenacoxib tablets, or a placebo. Drug was administered approximately 30 minutes prior to surgery along with pre-anesthetic medications and continued once daily for two additional treatments. Effectiveness was evaluated in 244 cats and field safety was evaluated in 249 cats. A statistically significant difference in the proportion of treatment successes in the robenacoxib tablets treatment group (137/164 or 83.5%) compared to the placebo, vehicle control group (43/80 or 53.8%) was observed. Twenty-seven out of 164 robenacoxib cases (16.5%) and 37 out of 80 placebo cases (46.2%) were treatment failures. Statistically significant differences for pain elicited on palpation at the spay or castration incision site, behavior following social interaction and posture score at various post-surgical time points were also observed. The results of the field study demonstrate that robenacoxib tablets, when administered for a maximum of three days, are effective and well-tolerated for the control of postoperative pain associated with onychectomy, ovariohysterectomy and castration in cats.

How Supplied:

Robenacoxib tablets are available as 6 mg round flavored tablets in blisters and are supplied in blister cards containing 3 tablets. The blister cards are supplied in a veterinary carton containing 10 blister cards and are to be dispensed 1 card per patient in a Robenacoxib tablets dispensing envelope containing veterinary insert and owner information sheet, supplied with the product.

Storage Conditions:

Store at 20° to 25°C (68° to 77°F), excursions permitted between 15° and 30°C (59° - 86°F).

Manufactured by:

Zydus Animal Health and Investments Limited,

Ahmedabad, India

Distributed by:

ZyVet Animal Health Inc.

Pennington, NJ 08534

References:

^1Giraudel, J.M., King J.N., Jeunesse, E.C., Lees, P. & Toutain, P.L. (2008). Use of a pharmacokinetic/pharmacodynamic approach in the cat to determine a dosage regimen for the COX-2 selective drug robenacoxib. J Vet Pharmacol Ther 2009;32:18-30.

^2Giraudel, J.M., Toutain, P.L., King J.N., & Lees, P. Differential inhibition of cyclooxygenase isoenzymes in the cat by the COX-2 selective drug robenacoxib. J Vet Pharmacol Ther 2009;32:31-40.

Approved by FDA under ANADA # 200-832

Robenacoxib

6 mg Tablets for Cats

For Oral Use In Cats Only

Information for Cat Owners - You should read this information before starting your cat on Robenacoxib tablets.

What is Robenacoxib?

Robenacoxib is a prescription non-narcotic, non-steroidal antiinflammatory (NSAID) of the coxib class. Robenacoxib is for the control of postoperative pain and inflammation associated with orthopedic surgery (declaw), ovariohysterectomy (spay) and castration (neuter) in cats greater than or equal to 5.5 pounds (2.5 kg) and greater than or equal to 4 months of age; for a maximum of 3 days. Do not use in cats less than 5.5 lbs.

Your cat may have received one or more doses of robenacoxib tablets or injection in the hospital. Your cat should not receive more than one dose a day, for a maximum of 3 total doses. Follow the instructions given to you by your veterinarian.

This summary contains important information about Robenacoxib but does not take the place of instructions from your veterinarian. Talk to your veterinarian if you do not understand any of this information or if you want to know more about Robenacoxib for cats.

What kind of results can I expect when my cat takes Robenacoxib for postoperative pain and inflammation?

Robenacoxib may help your cat to recover more comfortably by controlling postoperative pain and inflammation following orthopedic (declaw), ovariohysterectomy (spay), or castration surgery (neuter).

• Control of postoperative pain and inflammation may vary from cat to cat.

• Administer Robenacoxib tablets according to your veterinarian's directions, for a maximum of 3 days.

• Consult your veterinarian if your cat appears to be uncomfortable.

What cats should not take Robenacoxib?

Your cat should not be given Robenacoxib if s/he:

• Has had an allergic reaction to robenacoxib, the active ingredient in Robenacoxib for cats

• Has had an allergic reaction (such as hives, facial swelling, or red or itchy skin) to aspirin or other NSAIDs

• Is less than 5.5 lbs or less than 4 months of age

• Has a loss of appetite/decreased appetite

• Has bloody stool or vomit

• Is presently taking aspirin, other NSAIDs, or corticosteroids

• Has a pre-existing kidney or liver condition

• Has any condition predisposing to dehydration

Robenacoxib tablets should only be given to cats.

People should not take Robenacoxib tablets. Keep Robenacoxib tablets and all medication out of reach of children. Call your physician immediately if you accidentally take Robenacoxib tablets.

Keep Robenacoxib tablets in a secure location out of reach of dogs, cats, and other animals to prevent accidental ingestion or overdose.

Tell your veterinarian about:

• Any side effects your cat has previously experienced from Robenacoxib or other NSAIDs

• Any digestive upset (vomiting or diarrhea) your cat has had

• Any cardiovascular, kidney or liver disease your cat has had

• Any other medical problems or allergies that your cat has now or has had in the past

• All medications that you are giving your cat or plan to give your cat, including those you can get without prescription and any dietary supplements

• If you plan to breed your cat, or if your cat is pregnant or nursing

Talk to your veterinarian about:

• The surgery procedure performed on your cat

• What tests should be done before surgery and prior to administering Robenacoxib

• The signs of postoperative pain or inflammation that may occur following surgery

• Normal events that can be expected after your cat undergoes surgery

• How often your cat may need to be examined by your veterinarian

• The risks and benefits of using Robenacoxib

How to give Robenacoxib tablets to your cat.

Robenacoxib tablets should be given according to your veterinarian's instructions. Your veterinarian will tell you what amount of Robenacoxib tablets is right for your cat. Robenacoxib tablets should only be given once a day and for no longer than 3 days. Robenacoxib tablets should not be broken. Robenacoxib tablets should be given by mouth and may be given with or without food.

What are the possible side effects that may occur in my cat during therapy with Robenacoxib tablets?

Robenacoxib tablets may cause some side effects in individual cats. These are normally mild, but serious side effects have been reported in cats taking non-steroidal anti-inflammatory drugs (NSAIDs) including robenacoxib tablets. Serious side effects can result in death. It is important to stop the medication and contact your veterinarian immediately if you think your cat may have a medical problem or side effect while on Robenacoxib tablets. If you have additional questions about possible side effects, talk with your veterinarian or to report suspected adverse drug experiences, for technical assistance or to obtain a copy of the Safety Data Sheet (SDS), contact ZyVet Animal Health Inc. at 1-877-779-9838.

Look for the possible following side effects that may indicate that your cat is having a problem:

• Decrease in appetite

• Vomiting

• Change in bowel movements such as diarrhea or change in stool color

• Change in drinking or urination

• Change in behavior, such as depression or restlessness

If any of the above signs are noticed in your cat, stop administering Robenacoxib tablets and call your veterinarian.

Can Robenacoxib tablets be given with other medications?

Robenacoxib tablets should not be given with other non-steroidal antiinflammatory drugs (NSAIDs – i.e. aspirin, meloxicam) or corticosteroids (i.e. prednisone).

Always tell your veterinarian about all medications that you have given your cat in the past, and any medications that you are planning to give with Robenacoxib tablets.

What can I do in case my cat eats more than the prescribed amount of Robenacoxib tablets?

Contact your veterinarian immediately if your cat eats more than the prescribed amount of Robenacoxib tablets.

What else should I know about Robenacoxib tablets?

This sheet provides a summary of information about Robenacoxib tablets. If you have any questions or concerns about Robenacoxib or postoperative pain and inflammation, talk to your veterinarian.

As with all prescribed medications, Robenacoxib tablets should only be given to the cat for which they are prescribed. They should be given to your cat only for the condition for which they were prescribed, at the prescribed dose, as directed by your veterinarian.

Approved by FDA under ANADA # 200-832

Rev.: 11/25

PACKAGE LABEL.PRINCIPAL DISPLAY PANEL- Robenacoxib Cat 6 mg Dispensing Envelope

Robenacoxib

6 mg per

Tablet

Record date of when oral

or injectable dose(s) given

in hospital and when next

dose(s) are due.

Check box when dose is given.

6 mg

For oral use

in cats only.

≥ 5.5 pounds and

≥ 4 months of age

Date of Administration,

Robenacoxib given on

Day 1

Day 2

Day 3

GUJ/DRUGS/G/25/2354

Approved by FDA under ANADA # 200-832

Distributed by:

ZyVet Animal Health Inc. Pennington, NJ 08534

PACKAGE LABEL.PRINCIPAL DISPLAY PANEL-Robenacoxib Cat 6 mg Carton Label

Indication: For the control of postoperative pain and inflammation associated

with orthopedic surgery, ovariohysterectomy and castration, in cats ≥ 5.5 lbs

(2.5 kg) and ≥ 4 months of age; for up to a maximum of 3 days.

See product insert for complete information.

Robenacoxib

6 mg per

tablet

6mg

Keep this and all drugs out of the reach of children.

Keep Robenacoxib tablets in a secure location out of reach of dogs,

cats, and other animals to prevent accidental ingestion or overdose.

ZYVET

Animal Health